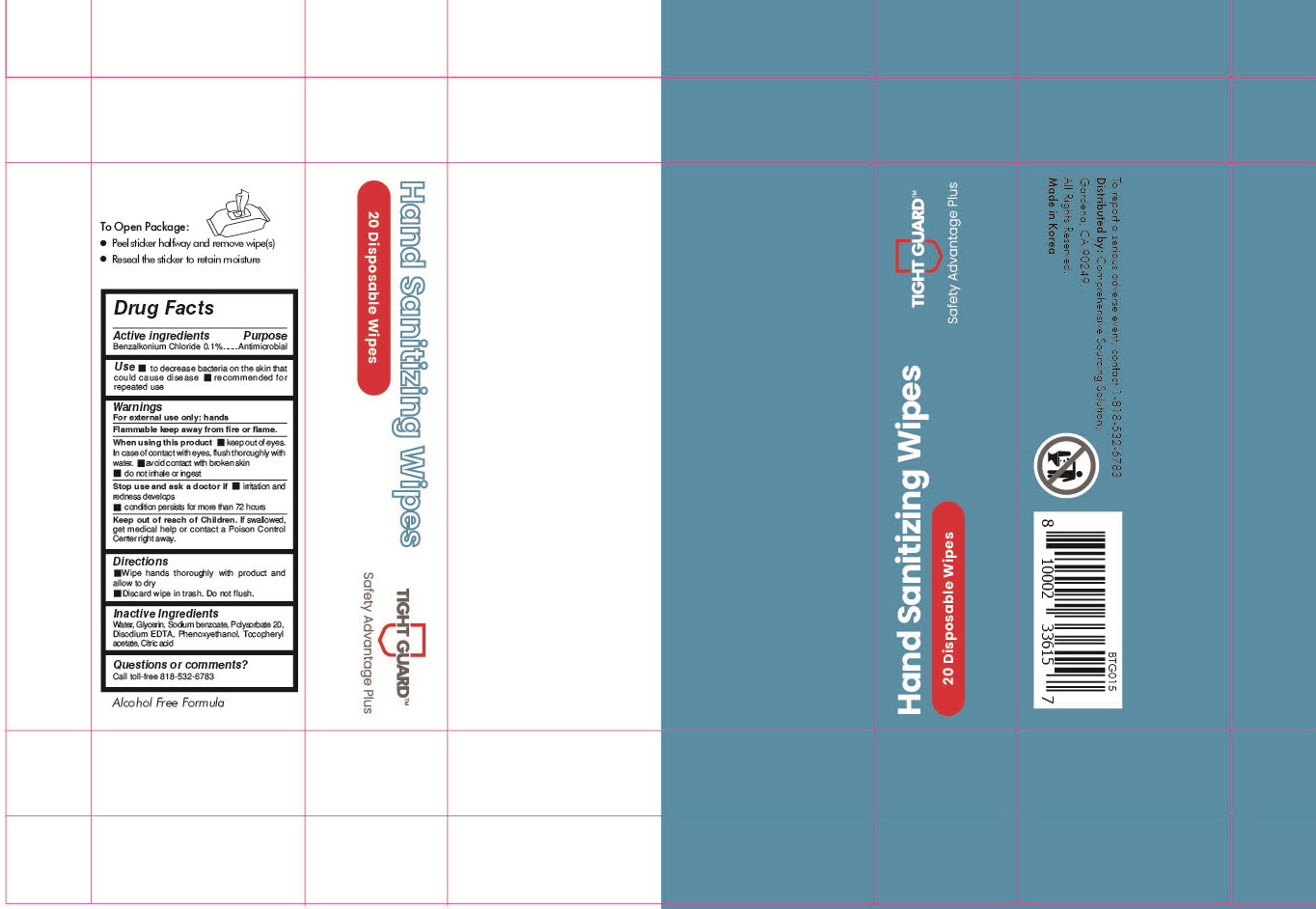 DRUG LABEL: TIGHT GUARD HAND SANITIZING WIPES
NDC: 76966-0011 | Form: CLOTH
Manufacturer: N Bridge Inc.
Category: otc | Type: HUMAN OTC DRUG LABEL
Date: 20200728

ACTIVE INGREDIENTS: BENZALKONIUM CHLORIDE 0.083 g/20 1
INACTIVE INGREDIENTS: PHENOXYETHANOL; EDETATE DISODIUM ANHYDROUS; SODIUM BENZOATE; WATER; CITRIC ACID MONOHYDRATE; GLYCERIN; POLYSORBATE 20; .ALPHA.-TOCOPHEROL ACETATE

ACTIVE INGREDIENT

benzalkonium chloride

INACTIVE INGREDIENT

water, disodium EDTA, sodium benzoate, glycerin, polysorbate 20, tocopheryl acetate, phenoxyethanol, citric acid

PURPOSE

Antiseptic

keep out of reach of the children

INDICATIONS AND USAGE

Wipe hands thoroughly with product and allow to dry.

Discard wipe in trash. Do not flush.

WARNINGS

For external use only. Flammable. Keep away from heat or flame.

When using this product

- keep out of eyes.
- in case of contact with eyes, flush thoroughly with water.
- avoid contact with broken skin
- do not inhale or ingest.

Stop use and ask a doctor if

- irritation and redness develops
- condition persists for more than 72 hours

Keep out of reach of children. If swallowed, get medical help or contact a Poison Control Center right away.

DOSAGE AND ADMINISTRATION

for external use only